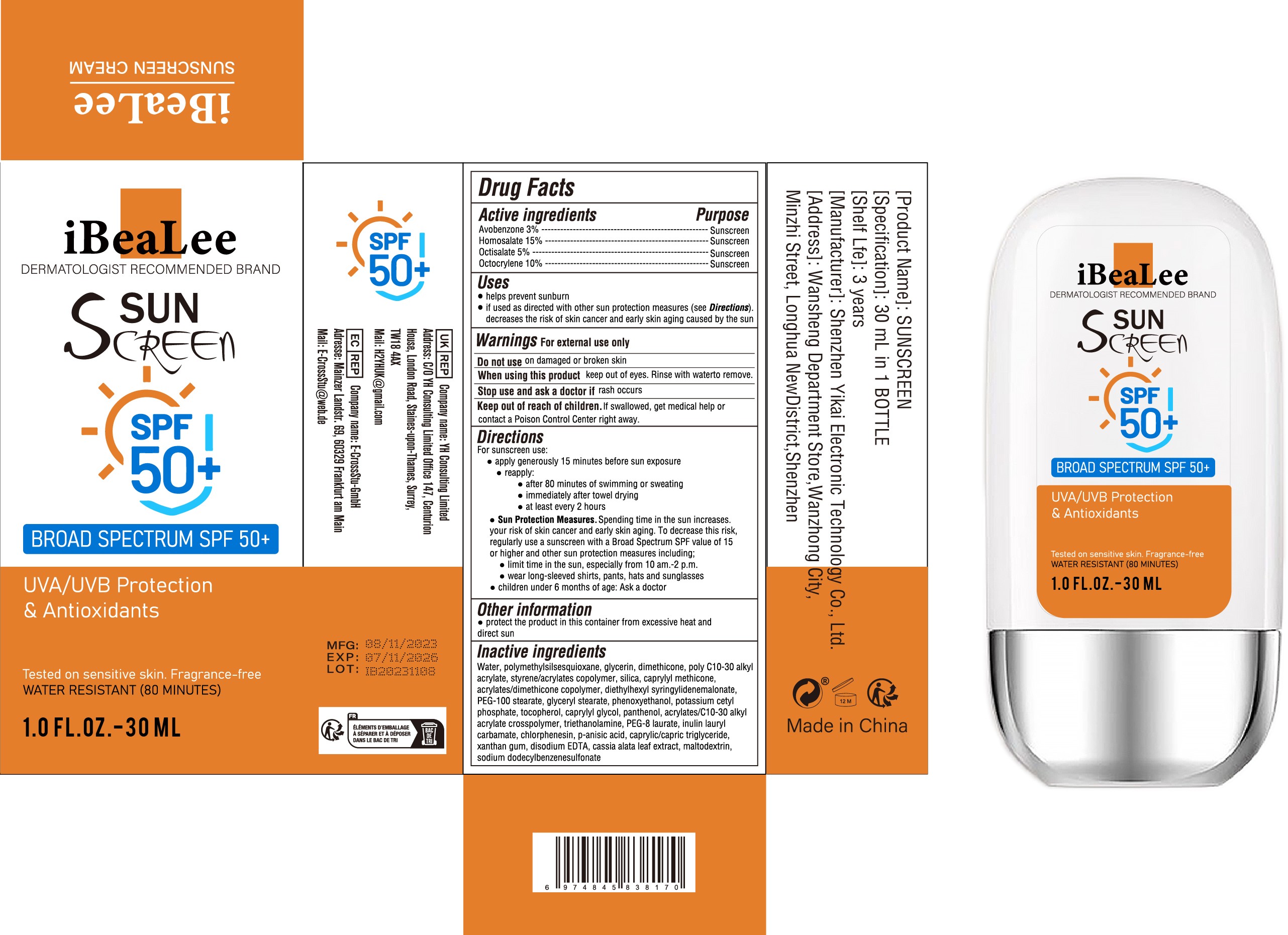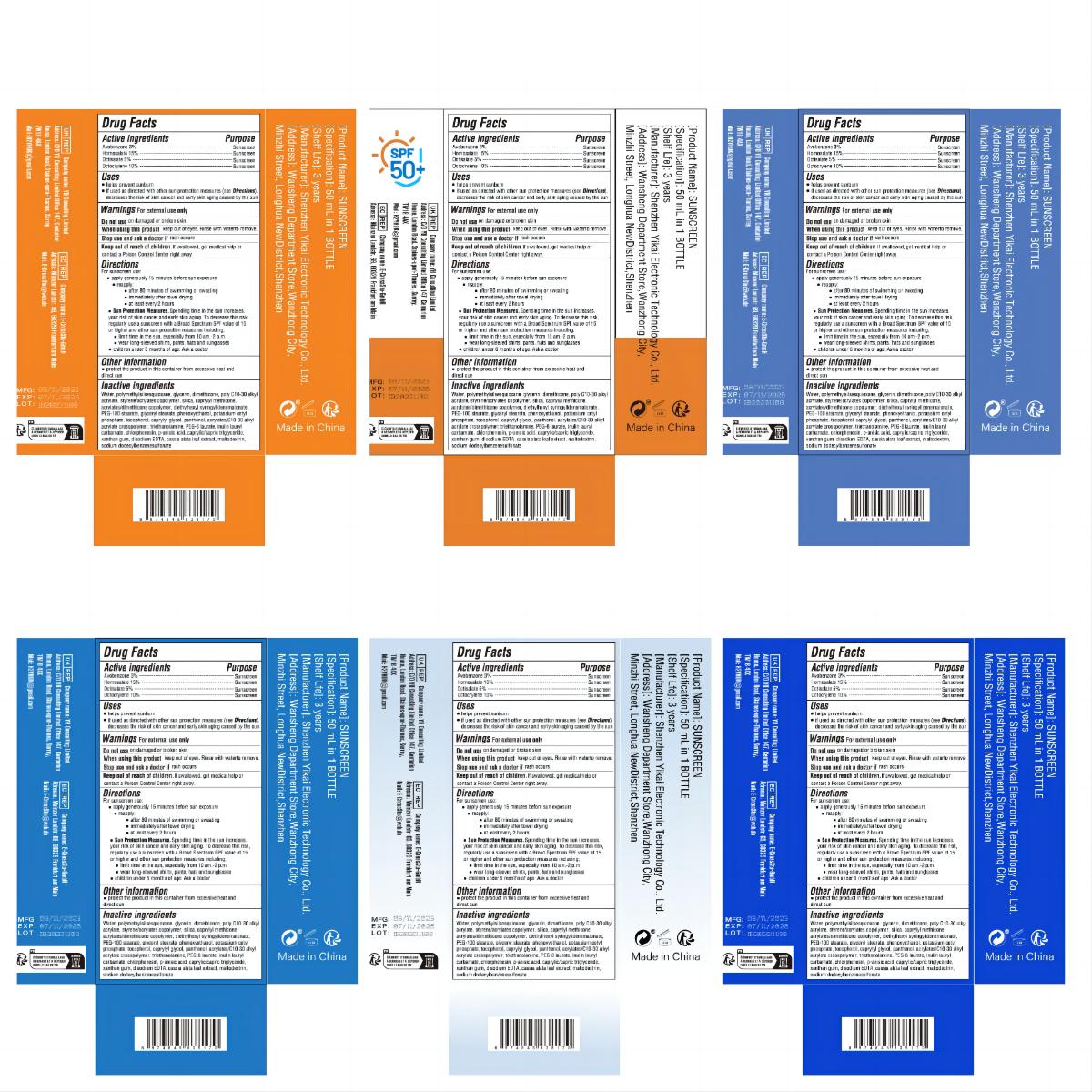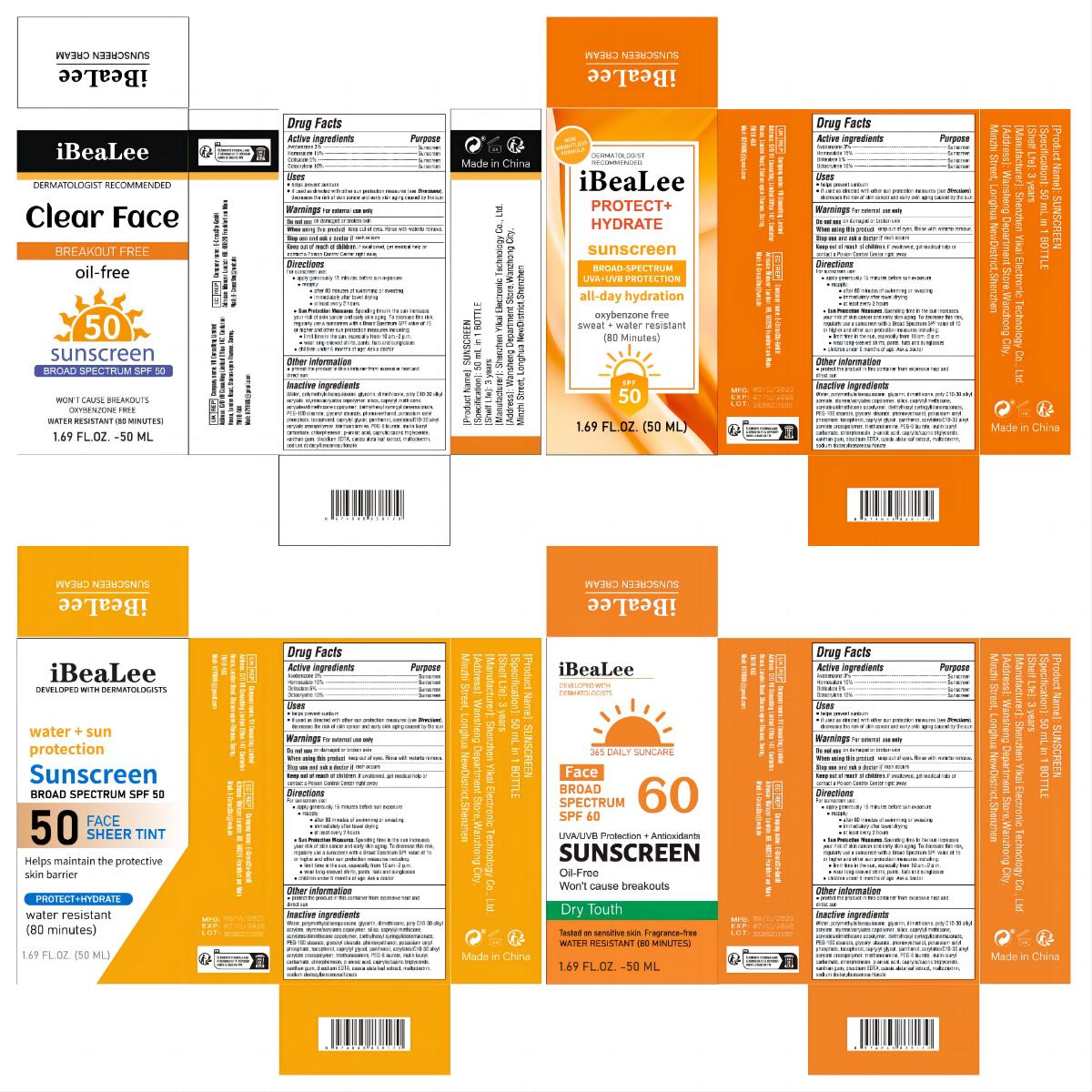 DRUG LABEL: SUNSCREEN
NDC: 83809-020 | Form: CREAM
Manufacturer: Shenzhen Yikai Electronic Technology Co., Ltd.
Category: otc | Type: HUMAN OTC DRUG LABEL
Date: 20240201

ACTIVE INGREDIENTS: OCTISALATE 5 g/100 mL; HOMOSALATE 15 g/100 mL; AVOBENZONE 3 g/100 mL; OCTOCRYLENE 10 g/100 mL
INACTIVE INGREDIENTS: GLYCERYL MONOSTEARATE; 2-ETHYLHEXYL ACRYLATE, METHACRYLATE, METHYL METHACRYLATE, OR BUTYL METHACRYLATE/HYDROXYPROPYL DIMETHICONE COPOLYMER (30000-300000 MW); DIETHYLHEXYL SYRINGYLIDENEMALONATE; CAPRYLYL GLYCOL; CHLORPHENESIN; EDETATE DISODIUM ANHYDROUS; BEHENYL ACRYLATE POLYMER; POLYOXYL 100 STEARATE; TOCOPHEROL; TROLAMINE; SENNA ALATA LEAF; GLYCERIN; DIMETHICONE; ACRYLIC ACID/2-ETHYLHEXYL ACRYLATE/STYRENE COPOLYMER (500000 MW); ACRYLATES/C10-30 ALKYL ACRYLATE CROSSPOLYMER (60000 MPA.S); XANTHAN GUM; WATER; POTASSIUM CETYL PHOSPHATE; PANTHENOL; PEG-8 LAURATE; INULIN LAURYL CARBAMATE; P-ANISIC ACID; MEDIUM-CHAIN TRIGLYCERIDES; MALTODEXTRIN; SODIUM DODECYLBENZENESULFONATE; POLYMETHYLSILSESQUIOXANE (4.5 MICRONS); SILICON DIOXIDE; CAPRYLYL TRISILOXANE; PHENOXYETHANOL

83809-020

Active Ingredient

Avobenzone 3%
Homosalate 15%
Octisalate 5%
Octocrylene 10%

Purpose

Sunscreen

Use

● helps prevent sunburn
● if used as directed with other sun protection measures (see Directions). decreases the risk of skin cancer and early skin aging caused by the sun

Warnings

For external use only

Do not use

on damaged or broken skin

When Using

keep out of eyes. Rinse with waterto remove.

Stop Use

rash occurs

Keep Oot Of Reach Of Children

lf swallowed, get medical help or contact a Poison Control Center right away.

Directions

For sunscreen use:
● apply generously 15 minutes before sun exposure
● reapply:
● after 80 minutes of swimming or sweating
● immediately after towel drying
● at least every 2 hours
● Sun Protection Measures. Spending time in the sun increases. your risk of skin cancer and early skin aging. To decrease this risk,
regularly use a sunscreen with a Broad Spectrum SPF value of 15 or higher and other sun protection measures including;
● limit time in the sun, especially from 10 am.-2 p.m.
● wear long-sleeved shirts, pants, hats and sunglasses
● children under 6 months of age: Ask a doctor

Other information

● protect the product in this container from excessive heat and direct sun

Inactive ingredients

Water, polymethylsilsesquioxane, glycerin, dimethicone, poly C10-30 alkyl
acrylate, styrene/acrylates copolymer, silica, caprylyl methicone,
acrylates/dimethicone copolymer, diethylhexyl syringylidenemalonate,
PEG-100 stearate, glyceryl stearate, phenoxyethanol, potassium cetyl
phosphate, tocopherol, caprylyl glycol, panthenol, acrylates/C10-30 alkyl
acrylate crosspolymer, triethanolamine, PEG-8 laurate, inulin lauryl
carbamate, chlorphenesin, p-anisic acid, caprylic/capric triglyceride,
xanthan gum, disodium EDTA, cassia alata leaf extract, maltodextrin,
sodium dodecylbenzenesulfonate